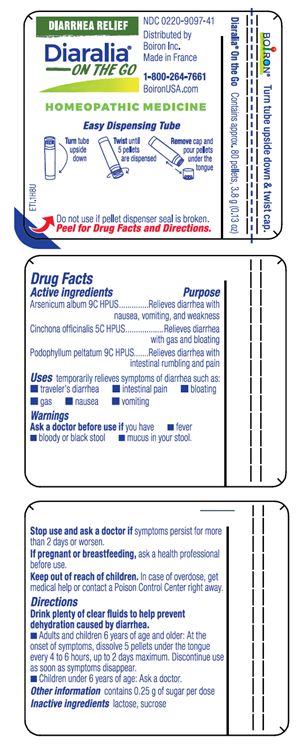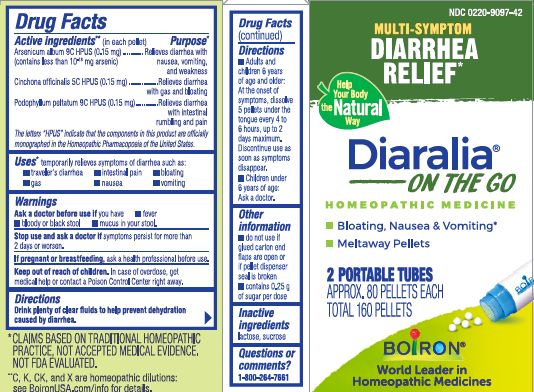 DRUG LABEL: DIARALIA
NDC: 0220-9097 | Form: PELLET
Manufacturer: Boiron
Category: homeopathic | Type: HUMAN OTC DRUG LABEL
Date: 20231004

ACTIVE INGREDIENTS: PODOPHYLLUM 9 [hp_C]/1 1; CINCHONA OFFICINALIS BARK 5 [hp_C]/1 1; ARSENIC TRIOXIDE 9 [hp_C]/1 1
INACTIVE INGREDIENTS: LACTOSE, UNSPECIFIED FORM; SUCROSE

Diaralia Pellets

Active ingredient** (in each pellet)

Arsenicum album 9C HPUS (0.15 mg) (contains less than 10^-18 mg arsenic)

Cinchona officinalis 5C HPUS (0.15 mg)

Podophyllum peltatum 9C HPUS (0.15 mg)

The letters "HPUS" indicate that the components in this product are officially monographed in the Homeopathic Pharmacopoeia of the United States.

Purpose*
Arsenicum album 9C HPUS (0.15 mg) .... Relieves diarrhea with nausea, vomiting, and weakness
Cinchona officinalis 5C HPUS (0.15 mg) ... Relieves diarrhea with gas and bloating
Podophyllum peltatum 9C HPUS (0.15 mg) ... Relieves diarrhea with intestinal rumbling and pain

Uses*

temporarily relieves symptoms of diarrhea such as:

- traveler's diarrhea
- intestinal pain
- bloating
- gas
- nausea
- vomiting

Ask a doctor before us if you have

- fever
- bloody or black stool
- mucus in your stool.

Stop use and ask a doctor if symptoms persist for more than 2 days or worsen.

PREGNANCY OR BREAST FEEDING

If pregnant or breastfeeding, ask a health professional before use.

Keep out of reach of children. In case of overdose, get medical help or contact a Poison Control Center right away.

DOSAGE AND ADMINISTRATION

Drink plenty of clear fluids to help prevent dehydration cause by diarrhea.

- Adults and children 6 years of age and older: At the onset of symptoms, dissolve 5 pellets under the tongue every 4 to 6 hours, up to 2 days maximum. Discontinue use as soon as symptoms disappear.
- Children under 6 years of age: Ask a doctor.

- do not use if glue carton end flaps are open or if pellet dispenser seal is broken
- contains 0.25 g of sugar per dose

Multi-symptom Diarrhea Relief*

Bloating, Nausea & Vomiting*

Meltaway Pellets

2 PORTABLE TUBES

APPROX. 80 PELLETS EACH

TOTAL 160 PELLETS

Contains approx. 80 pellets, 3.8 g (0.13 oz)

Do not use if pellet dispenser seal is broken.

Turn tube upside down

Twist until 5 pellets are dispensed

Remove cap and pour pellets under the tongue

Turn tube upside down & twist cap

*CLAIMS BASED ON TRADITIONAL HOMEOPATHIC PRACTICE NOT ACCEPTED MEDICAL EVIDENCE. NOT FDA EVALUATED.
**C,K,CK, and X are homeopathic dilutions: see BoironUSA.com/info for details.

INACTIVE INGREDIENT

lactose, sucrose

QUESTIONS

1-800-264-7661
Made in France
Distributed by Boiron, Inc.
Newtown Square, PA
19073